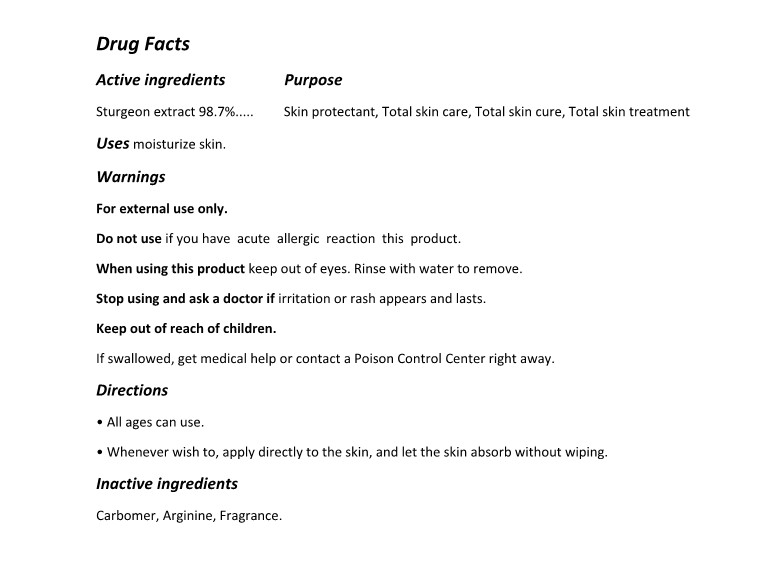 DRUG LABEL: The Zoeun Skin Total Care Cream
NDC: 83636-201 | Form: CREAM
Manufacturer: Sturgeonbio Co.,Ltd.
Category: otc | Type: HUMAN OTC DRUG LABEL
Date: 20250120

ACTIVE INGREDIENTS: STURGEON, UNSPECIFIED 98.7 g/100 mL
INACTIVE INGREDIENTS: FRAGRANCE FLORAL ORC0902236; CARBOMER HOMOPOLYMER, UNSPECIFIED TYPE; ARGININE

83636-201 The Zoeun Skin Total Care Cream

Active Ingredients

Sturgeon

Purposes

Skin protectant, Total skin care, Total skin cure, Total skin treatment

Uses

moisturize skin

Warnings

For external use only

Warnings

Do not use on damaged or broken skin

Warnings

Keep out of reach of children

If swallowed, get medical help or contact a Poison Control Center right away

Warnings

Stop using and ask a doctor if irritation or rash appears and lasts

Warnings

When using this product keep out of eyes. Rinse with water to remove

Directions

• All ages can use.

• Whenever wish to, apply directly to the skin, and let the skin absorb without wiping.

Inactive Ingredients

Carbomer, Arginine, Fragrance